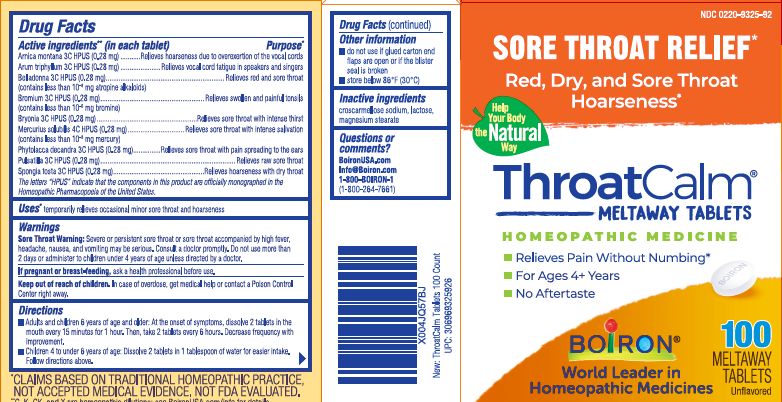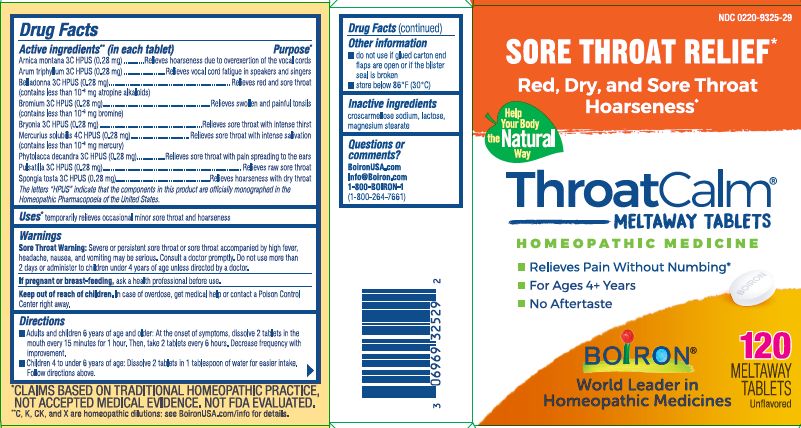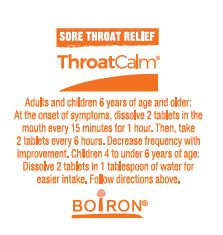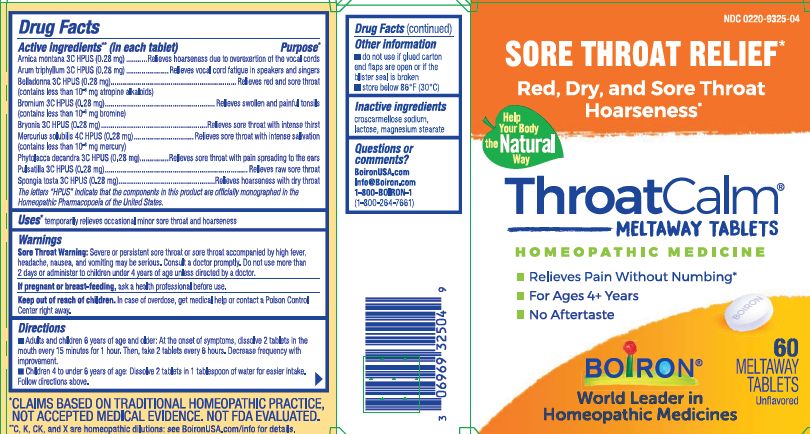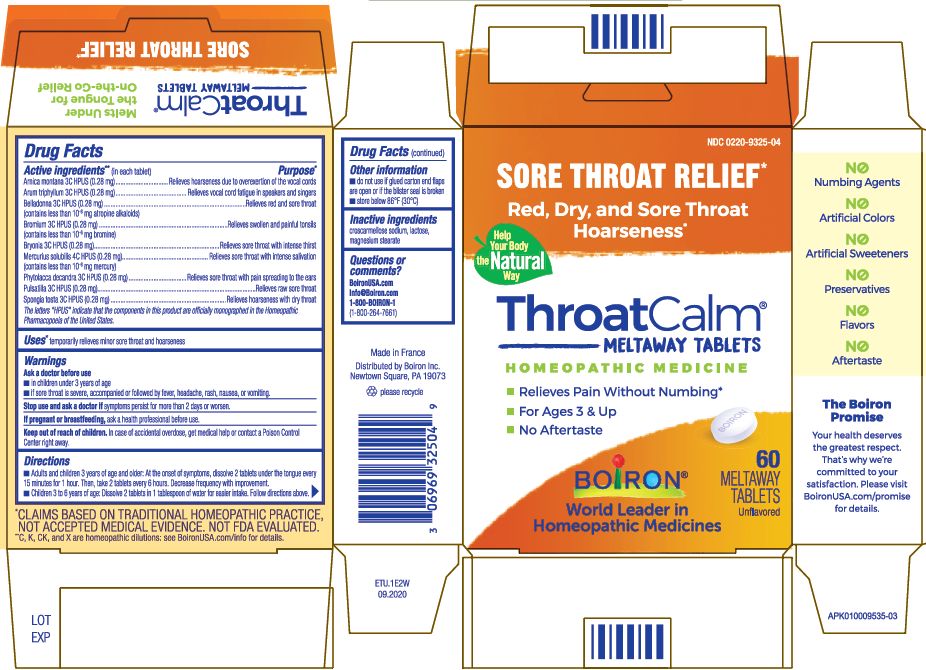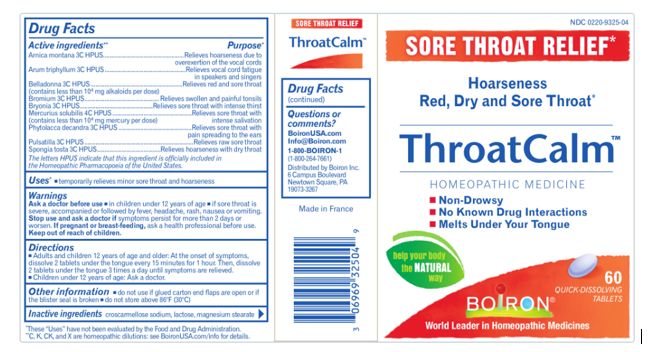 DRUG LABEL: ThroatCalm
NDC: 0220-9325 | Form: TABLET
Manufacturer: Laboratoires Boiron
Category: homeopathic | Type: HUMAN OTC DRUG LABEL
Date: 20250317

ACTIVE INGREDIENTS: ARNICA MONTANA 3 [hp_C]/1 1; ARISAEMA TRIPHYLLUM ROOT 3 [hp_C]/1 1; BELLADONNA LEAF 3 [hp_C]/1 1; BROMINE 3 [hp_C]/1 1; BRYONIA ALBA ROOT 3 [hp_C]/1 1; SPONGIA OFFICINALIS SKELETON, ROASTED 3 [hp_C]/1 1; MERCURIUS SOLUBILIS 4 [hp_C]/1 1; PHYTOLACCA AMERICANA ROOT 3 [hp_C]/1 1; PULSATILLA VULGARIS 3 [hp_C]/1 1
INACTIVE INGREDIENTS: CROSCARMELLOSE SODIUM; LACTOSE; MAGNESIUM STEARATE

ThroatCalm

Active Ingredients

Active ingredients** (in each tablet)

Arnica montana 3C HPUS (0.28 mg)

Arum triphyllum 3C HPUS (0.28 mg)

Belladonna 3C HPUS (0.28 mg) (contains less than 10^-8 mg atropine alkaloids)

Bromium 3C HPUS (0.28 mg) (contains less than 10^-6 mg bromine)

Bryonia 3C HPUS (0.28 mg)

Mercurius solubilis 4C HPUS (0.28 mg) (contains less than 10^-8 mg mercury)

Phytolacca decandra 3C HPUS (0.28 mg)

Pulsatilla 3C HPUS (0.28 mg)

Spongia tosta 3C HPUS (0.28 mg)

The letters "HPUS" indicate that the components in this product are officially monographed in the Homeopathic Pharmacopoeia of the United States.

Purpose

Arnica montana 3C HPUS ... Relieves hoarseness due to overexertion of the vocal cords
Arum triphyllum 3C HPUS ... Relieves vocal cord fatigue in speakers and singers
Belladonna 3C HPUS ... Relieves red and sore throat
Bromium 3C HPUS ... Relieves swollen and painful tonsils
Bryonia 3C HPUS ... Relieves sore throat with intense thirst
Mercuris solubilis 4C HPUS ... Relieves sore throat with intense salivation
Phytolacca decandra 3C HPUS ... Relieves sore throat with pain spreading to the ears
Pulsatilla 3C HPUS ... Relieves raw sore throat
Spongia tosta 3C HPUS ... Relieves hoarseness with dry throat

Uses

temporarily relieves occasional minor sore throat and hoarseness

WARNINGS

Sore Throat Warning: Severe or persistent sore throat or sore throat accompanied by high fever, headache, nausea, and vomiting may be serious. Consult a doctor promptly. Do not use more than 2 days or administer to children 4 years of age unless directed by a doctor.

PREGNANCY OR BREAST FEEDING

If pregnant or breast-feeding, ask a health professional before use.

Keep out of reach of children. In case of overdose, get medical help or contact a Poison Control Center right away.

Directions

Adults and children 6 years of age and older: At the onset of symptoms, dissolve 2 tablets in the mouth every 15 minutes for 1 hour. Then, take 2 tablets every 6 hours. Decrease frequency with improvement.
Children 4 to under 6 years of age: Dissolve 2 tablets in 1 tablespoon of water for easier intake. Follow directions above.

Other information

do not use if glued carton end flaps are open or if the blister seal is broken
do not store above 86o F (30o C)

Inactive Ingredient

croscarmellose sodium, lactose, magnesium stearate

Questions or comments?

BoironUSA.com
info@boironusa.com
1-800-BOIRON-1 (1-800-264-7661)
Distributed by Boiron Inc.
Newtown Square, PA 19073

do not use if glued carton end flaps are open or if the blister seal is broken
do not store above 86oF (30oC)

Sore Throat Relief*

Red, Dry,and Sore Throat Hoarseness*

Relieves Pain Without Numbing*

For Ages 4+ Years

No Aftertaste

60 Meltaway tablets unflavored

100 Meltaway tablets unflavored

120 Meltaway tablets unflavored

*CLAIMS BASED ON TRADITIONAL HOMEOPATHIC PRACTICE, NOT ACCEPTED MEDICAL EVIDENCE. NOT FDA EVALUATED.
*C,K,CK, and X are homeopathic dilutions: see BoironUSA.com/info for details.